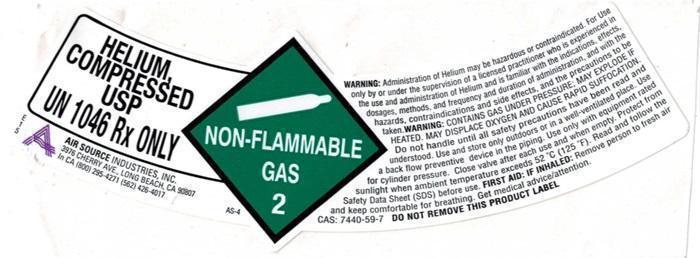 DRUG LABEL: HELIUM
NDC: 10167-300 | Form: GAS
Manufacturer: Air Source Industries Inc
Category: prescription | Type: HUMAN PRESCRIPTION DRUG LABEL
Date: 20241006

ACTIVE INGREDIENTS: HELIUM 99 L/100 L

Helium

HELIUM COMPRESSED Product Label

HELIUM COMPRESSED USP UN 1046

E15 A Air Source Industries, Inc.

3976 CHERRY AVE., LONG BEACH, CA 90807

In CA (800) 295-4271 (562) 426-4017 AS-4

NON-FLAMMABLE GAS 2

WARNING: Administration of Helium may be hazardous or contraindicated. For use only by or under the supervision of a licensed practitioner who is experienced in the use and administration of Helium and is familiar with the indications, effects, dosages, methods, and frequency and
duration of administration and with hazards, contraindications, and side effects and the precautions to be taken.

WARNING:CONTAINSGAS UNDER PRESSURE; MAT EXPLODEIF HEATED. MAY DISPLACE OXYGEN AND CAUSE RAPID SUFFOCATION. Do not handle until all safety precautions have been read and understood. Use and store only outdoors or in a well-ventilated place. Use a back flow prevention device in the piping. Use only with equipment rated for cylinder pressure. Close valve after each use and when empty. Protect from sunlight when ambient temperature exceeds 52°C (125°F). Read and follow the Safety Data Sheet (SDS) before use. FIRST AID: IF INHALED: Remove person to fresh air and keep comfortable for breathing. Get medical advice/attention.

CAS: 7440-59-7 DO NOT REMOVE THIS PRODUCT LABEL